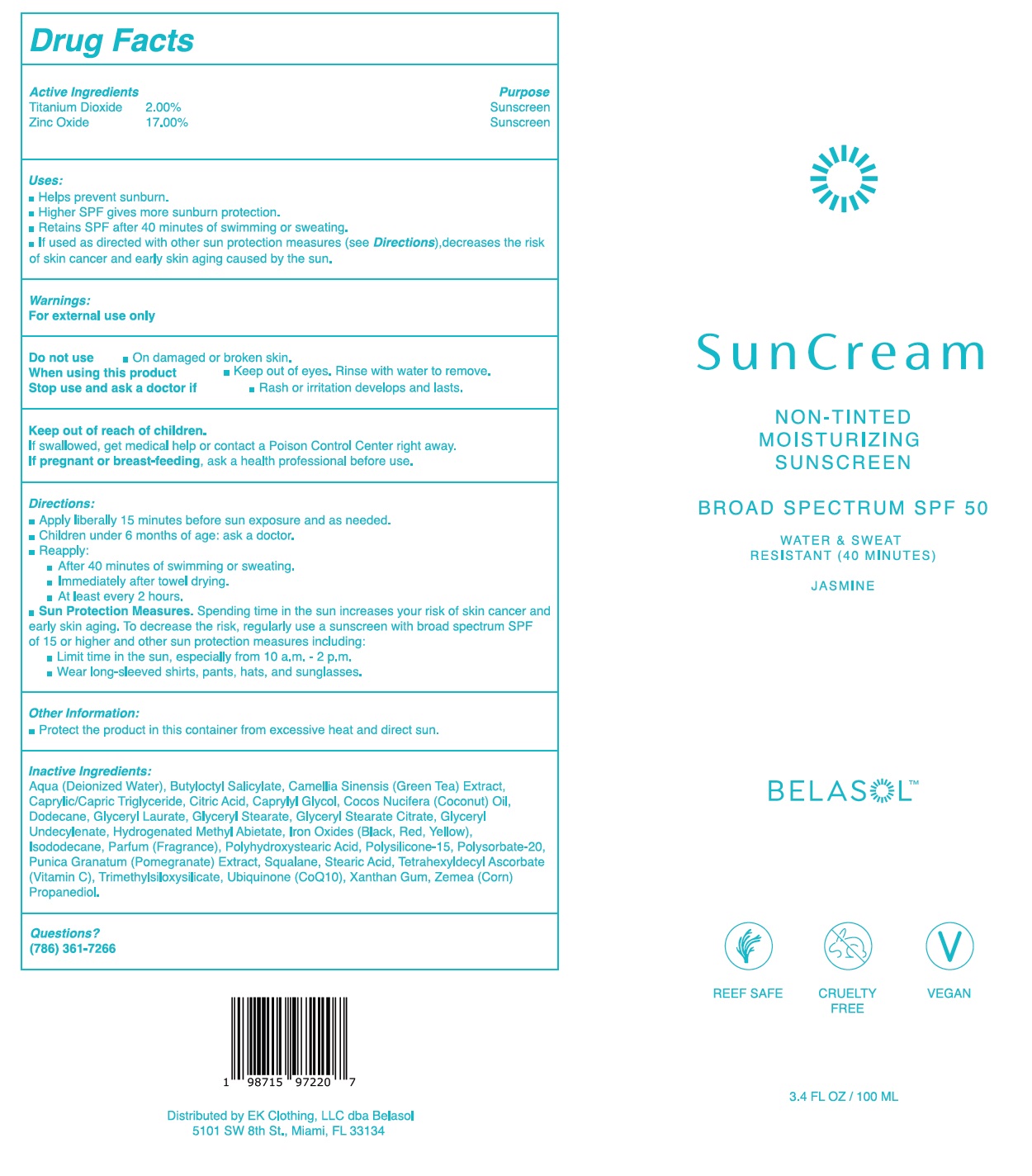 DRUG LABEL: Belasol Suncream Non Tinted Moisturizing Sunscreen SPF 50 Jasmine
NDC: 83789-572 | Form: CREAM
Manufacturer: EK Clothing LLC dba Belasol
Category: otc | Type: HUMAN OTC DRUG LABEL
Date: 20241218

ACTIVE INGREDIENTS: TITANIUM DIOXIDE 20 mg/1 mL; ZINC OXIDE 170 mg/1 mL
INACTIVE INGREDIENTS: WATER; BUTYLOCTYL SALICYLATE; GREEN TEA LEAF; CAPRYLIC/CAPRIC TRIGLYCERIDE; CITRIC ACID; CAPRYLYL GLYCOL; COCOS NUCIFERA (COCONUT) OIL; DODECANE; GLYCERYL LAURATE; GLYCERYL STEARATE; GLYCERYL STEARATE CITRATE; HYDROGENATED METHYL ABIETATE; FERROSOFERRIC OXIDE; FERRIC OXIDE RED; FERRIC OXIDE YELLOW; ISODODECANE; POLYSILICONE-15; POLYSORBATE 20; POMEGRANATE; SQUALANE; STEARIC ACID; ASCORBIC ACID; UBIDECARENONE; XANTHAN GUM; CORN

Belasol Suncream Non-Tinted Moisturizing Sunscreen SPF 50 Jasmine

Active Ingredients

Titanium Dioxide 2.00%

Zinc Oxide 17.00%

Purpose

Sunscreen

Uses:

- Helps prevent sunburn.
- Higher SPF gives more sunburn protection.
- Retains SPF after 40 minutes of swimming or sweating.
- If used as directed with other sun protection measures (see Directions), decreases the risk of skin cancer and early skin aging caused by the sun.

Warnings:

For external use only

Do not use

- On damaged or broken skin.

When using this product

- Keep out of eyes. Rinse with water to remove.

Stop use and ask a doctor if

- Rash or irritation develops and lasts.

Keep out of reach of children.

If swallowed, get medical help or contact a Poison Control Center right away.

If pregnant or breast-feeding,

ask a health professional before use.

Directions

- Apply liberally 15 minutes before sun exposure and as needed.
- Children under 6 months of age: ask a doctor.
- Reapply:
- After 40 minutes of swimming or sweating.
- Immediately after towel drying.
- At least every 2 hours.
- Sun Protection Measures.Spending time in the sun increases your risk of skin cancer and early skin aging. To decrease the risk, regularly use a sunscreen with broad spectrum SPF of 15 or higher and other sun protection measures including:
- Limit time in the sun, especially from 10 a.m. - 2 p.m.
- Wear long-sleeved shirts, pants, hats, and sunglasses.

Other Information

- Protect the product in this container from excessive heat and direct sun.

Inactive Ingredients:

Aqua (Deionized Water), Butyloctyl Salicylate, Camellia Sinensis (Green Tea) Extract, Caprylic/Capric Triglyceride, Citric Acid, Caprylyl Glycol, Cocos Nucifera (Coconut) Oil, Dodecane, Glyceryl Laurate, Glyceryl Stearate, Glyceryl Stearate Citrate, Glyceryl Undecylenate, Hydrogenated Methyl Abietate, Iron Oxides (Black, Red, Yellow), Isododecane, Parfum (Fragrance), Polyhydroxystearic Acid, Polysilicone-15, Polysorbate-20, Punica Granatum (Pomegranate) Extract, Squalane, Stearic Acid, Tetrahexyldecyl Ascorbate (Vitamin C), Trimethylsiloxysilicate, Ubiquinone (CoQ10), Xanthan Gum, Zemea (Corn) Propanediol.

Questions?

(786) 361-7266